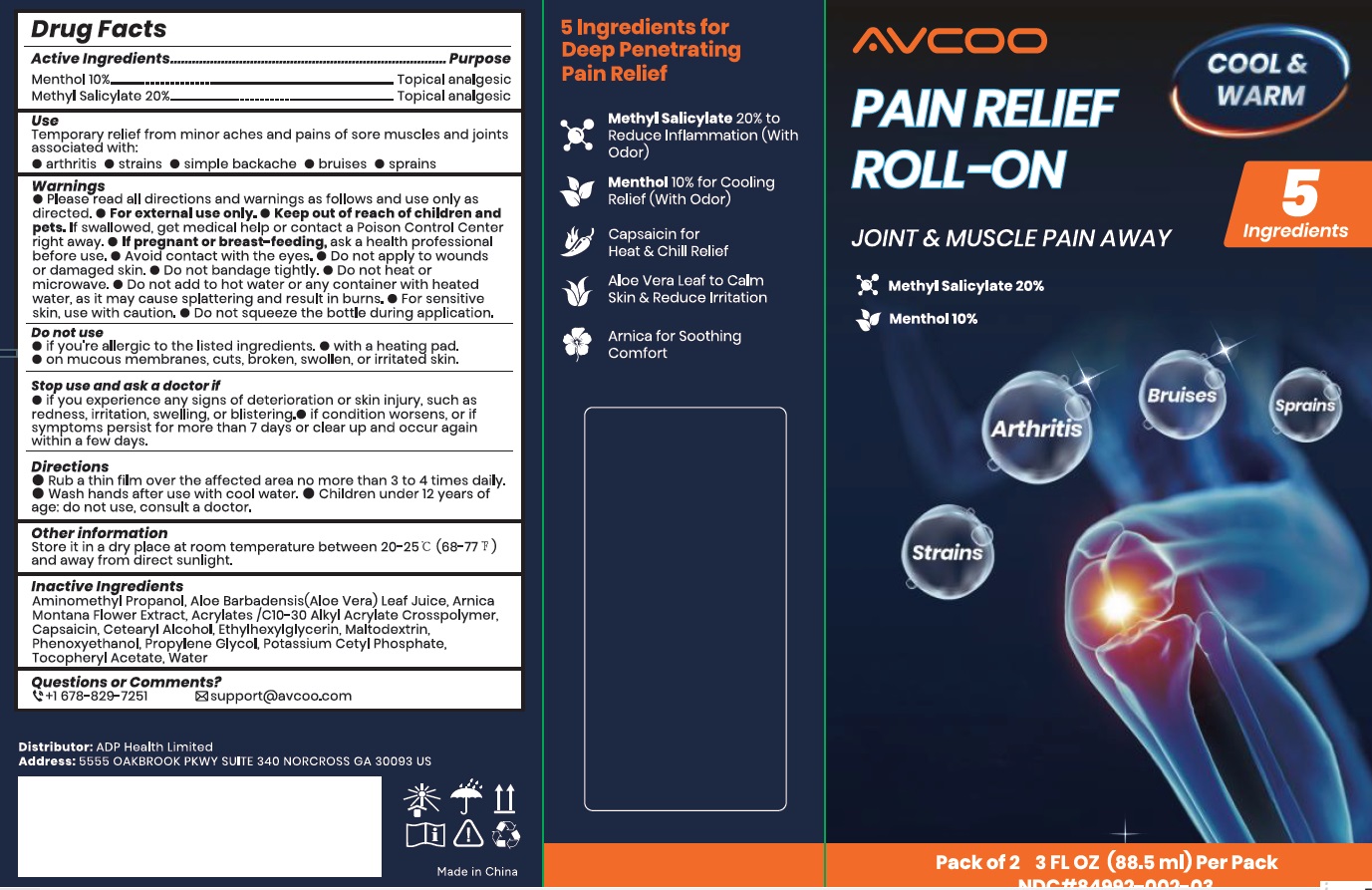 DRUG LABEL: AVCOO Pain Relief Roll On
NDC: 84992-002 | Form: CREAM
Manufacturer: ADP Health Limited
Category: otc | Type: HUMAN OTC DRUG LABEL
Date: 20250219

ACTIVE INGREDIENTS: MENTHOL 10 g/100 mL; METHYL SALICYLATE 20 g/100 mL
INACTIVE INGREDIENTS: WATER; ALOE VERA LEAF; CAPSAICIN; AMINOMETHYLPROPANOL; ACRYLATES/C10-30 ALKYL ACRYLATE CROSSPOLYMER (60000 MPA.S AT 0.5%); ARNICA MONTANA FLOWER WATER; CETEARYL ALCOHOL; ETHYLHEXYLGLYCERIN; MALTODEXTRIN; PHENOXYETHANOL; PROPYLENE GLYCOL; POTASSIUM CETYL PHOSPHATE; .ALPHA.-TOCOPHEROL ACETATE

84992-002 AVCOO Menthol and Methyl Salicylate Pain relief Roll-on

Active ingredient

Menthol 10%

Methyl Salicylate: 20%

Purpose

Topical Analgesic

Uses

Temporary relief from minor aches and pains of sore muscles and joints associatedly with:

simple backaches, arthritis, strains, bruises, and sprain

Warnings

- Please read all directions and warnings as follows and use only as directed. For external use only.
- Flammable:Keep away from excessive heat and open flame
- Do not heat or microwave
- Do not add to hot water or any container with heated water, as it may cause splattering and resultin burns
- Do not bandage tightly
- Avoid contact with eyes
- For sensitive skins, use with caution
- So not squeeze the bottle during application

Keep out of reach of children or pets. If swallowed, get medical help or contact a Poison Control Center right away

PREGNANCY

If pregnant or breast-feeding,ask a healthcare professional before use

Do not use

- if you are allergic to the listed ingredients
- with a heating pad
- on mucous membrances, cuts, broken, swollen, or irritated skin

Stop Use and Ask a Doctor

- if you experience any signs of deterioration or skin injury, such as redness, irritation, swelling, and blistering
- if condition worsens, or if syptoms persist for more than 7 days or clear up and occur again within a few days.

Directions

- Rub a thin film over the affected area no more than 3-4 times daily
- Wash hands after use with cold water
- Children under 12 years of age: do not use, consult a doctor

Other Information

- store in a dry place at room temperature between 20-25C (77-86F) and away from direct sunlight

Inactive ingredients

Aminomethyl Propanol, Aloe Barbadensis Leaf Juice, Arnica Montana Flower Extract, Acrylates /C10-30 Alkyl Acrylate Crosspolymer, Capsaicin, Cetearyl Alcohol, Ethylhexylglycerin, Maltodextrin, Phenoxyethanol, Propylene Glycol, Potassium Cetyl Phosphate, Tocopheryl Acetate, Water